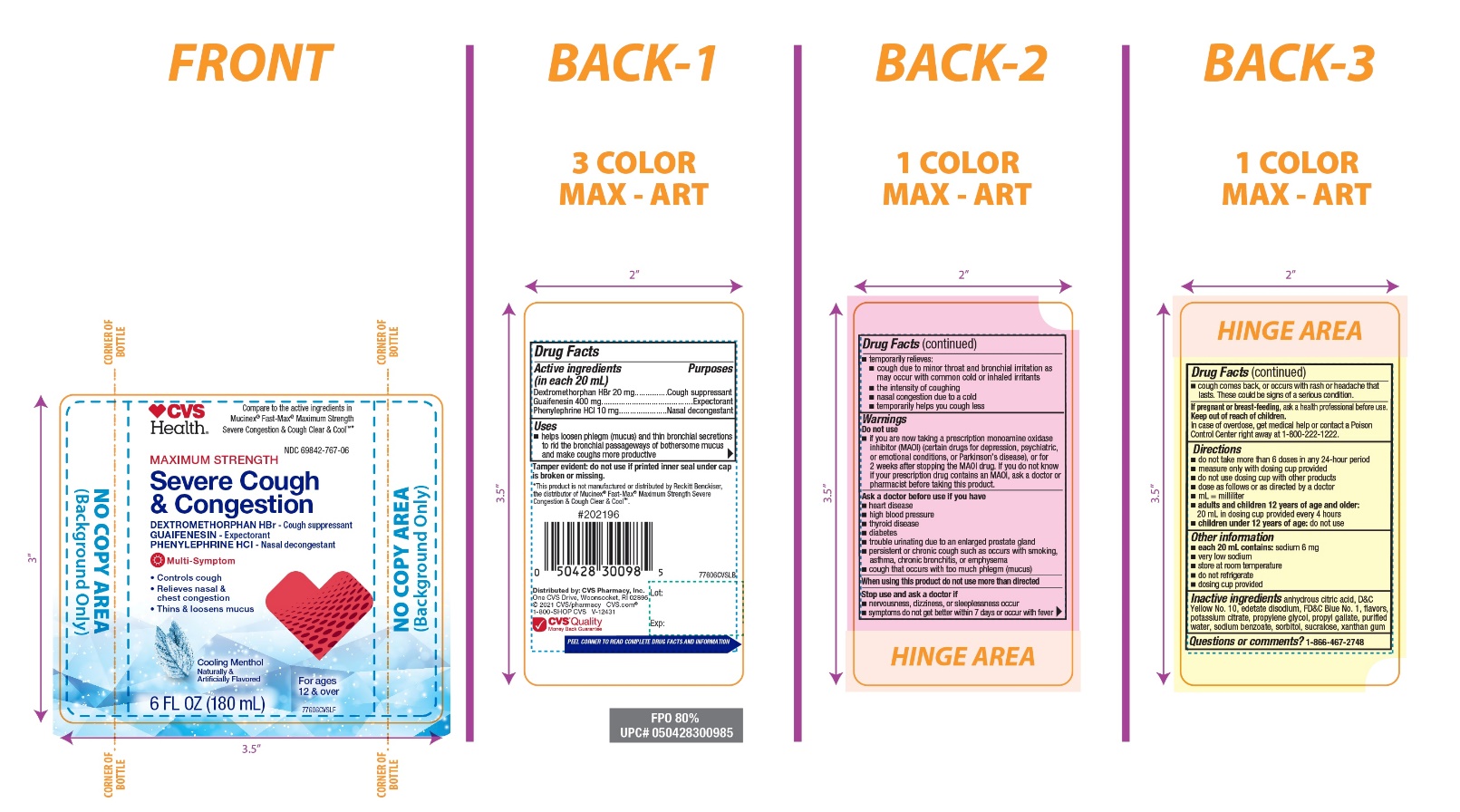 DRUG LABEL: CVS Maximum Strength Severe Congestion and Cough
NDC: 69842-767 | Form: LIQUID
Manufacturer: CVS PHARMACY, INC
Category: otc | Type: HUMAN OTC DRUG LABEL
Date: 20251210

ACTIVE INGREDIENTS: DEXTROMETHORPHAN HYDROBROMIDE 20 mg/20 mL; GUAIFENESIN 400 mg/20 mL; PHENYLEPHRINE HYDROCHLORIDE 10 mg/20 mL
INACTIVE INGREDIENTS: ANHYDROUS CITRIC ACID; D&C YELLOW NO. 10; EDETATE DISODIUM; FD&C BLUE NO. 1; POTASSIUM CITRATE; PROPYLENE GLYCOL; PROPYL GALLATE; WATER; SODIUM BENZOATE; SORBITOL; SUCRALOSE; XANTHAN GUM

CVS Maximum Strength Severe Congestion and Cough Cooling Menthol Flavor

Drug Facts

ACTIVE INGREDIENT

PURPOSE

Active ingredients (in each 20 mL) | Purposes
Dextromethorphan HBr 20 mg | Cough suppressant
Guaifenesin 400 mg | Expectorant
Phenylephrine HCl 10 mg | Nasal decongestant

Uses

- helps loosen phlegm (mucus) and thin bronchial secretions to rid the bronchial passageways of bothersome mucus and make coughs more productive
- temporarily relieves:
  - cough due to minor throat and bronchial irritation as may occur with the common cold or inhaled irritants
  - the intensity of coughing
  - nasal congestion due to a cold
  - temporarily helps you cough less

Warnings

Do not use

- if you are now taking a prescription monoamine oxidase inhibitor (MAOI) (certain drugs for depression, psychiatric, or emotional conditions, or Parkinson's disease), or for 2 weeks after stopping the MAOI drug. If you do not know if your prescription drug contains an MAOI, ask a doctor or pharmacist before taking this product.

Ask a doctor before use if you have

- heart disease
- high blood pressure
- thyroid disease
- diabetes
- trouble urinating due to an enlarged prostate gland
- persistent or chronic cough such as occurs with smoking, asthma, chronic bronchitis or emphysema
- cough that occurs with too much phlegm (mucus)

Stop use and ask a doctor if

- nervousness, dizziness or sleeplessness occur
- symptoms do not get better within 7 days or occur with fever
- cough comes back, or occurs with rash or headache that lasts. These could be signs of a serious condition.

PREGNANCY OR BREAST FEEDING

If pregnant or breast-feeding,ask a health professional before use.

Keep out of reach of children.In case of overdose, get medical help or contact a Poison Control Center right away at (1-800-222-1222).

Directions

- do not take more than 6 doses in any 24-hour period
- measure only with dosing cup provided
- do not use dosing cup with other products
- dose as follows or as directed by a doctor
- mL = milliliter
- adults and children 12 years of age and older:20 mL in dosing cup provided every 4 hours.
- children under 12 years of age:Do not use.

Other information

- each 20 mL contains:sodium 6 mg
- very low sodium
- store at room temperature
- do not refrigerate
- dosing cup provided

Inactive Ingredients

anhydrous citric acid, D&C Yellow No. 10, edetate disodium, FD&C Blue No. 1, flavor, potassium citrate, propylene glycol, propyl gallate, purified water, sodium benzoate, sorbitol, sucralose, xanthan gum.

Questions or comments?

1-866-467-2748

PRINCIPAL DISPLAY PANEL

NDC# 69842-767-06

Compare to Mucinex®Fast-Max®Maximum Strength Severe Congestion & Cough Clear and Cool®Active Ingredients*

Maximum Strength

Severe Congestion & Cough

- Dextromethorphan HBrCough Suppressant
  GuaifenesinExpectorant
  Phenylephrine HClNasal Decongestant

1. Controls Cough,
2. Relieves Nasal & Chest Congestion
3. Thins & Loosens Mucus

Cooling Menthol Flavor

Naturally and Artificially Flavored

6 FL OZ (180 mL)

For Ages 12+

Tamper evident: do not use if printed seal under cap is broken or missing.

Distributed by:

*This product is not manufactured or distributed by Reckitt Benckiser, the distributor of Mucinex® Fast -Max® Maximum Strength Severe Congestion & Cough Clear & Cool™.